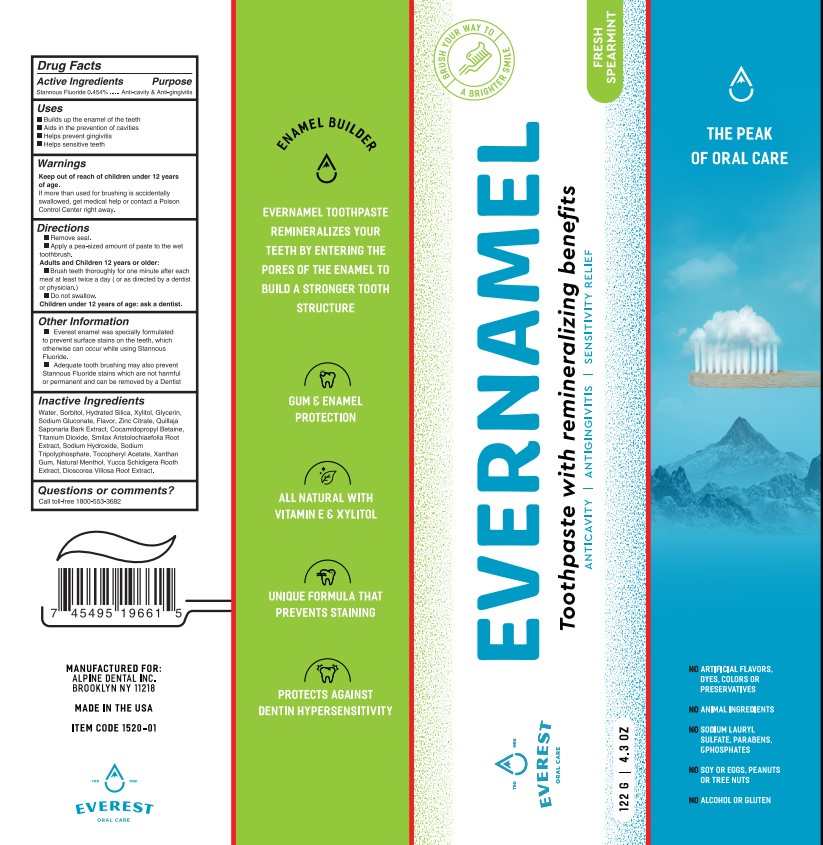 DRUG LABEL: Evernamel
NDC: 83199-102 | Form: PASTE, DENTIFRICE
Manufacturer: Alpine Dental, Inc.
Category: otc | Type: HUMAN OTC DRUG LABEL
Date: 20230123

ACTIVE INGREDIENTS: STANNOUS FLUORIDE 0.454 mg/100 g
INACTIVE INGREDIENTS: WATER; SORBITOL; HYDRATED SILICA; XYLITOL; GLYCERIN; SODIUM GLUCONATE; ZINC CITRATE; QUILLAJA SAPONARIA BARK; COCAMIDOPROPYL BETAINE; TITANIUM DIOXIDE; SMILAX ARISTOLOCHIIFOLIA ROOT; SODIUM HYDROXIDE; SODIUM TRIPOLYPHOSPHATE; .ALPHA.-TOCOPHEROL ACETATE; XANTHAN GUM; MENTHOL; YUCCA SCHIDIGERA ROOT; DIOSCOREA VILLOSA WHOLE

Active Ingredients

Stannous Fluoride, 0.454%

Purpose

Anti-cavity & Anti-gingivitis

Uses

• Builds up the enamel of teeth
• Aids in the prevention of cavities
• Helps prevent gingivitis
• Helps sensitive teeth

Keep out of reach of children under 12 years of age.
If more than used for brushing is accidentally swallowed, get medical help or contact a Poison Control Center right away.

Directions

• Remove seal
• Apply a pea-sized amount of paste to the wet toothbrush

Adults and Children 12 years or older:
• Brush teeth thoroughly for one minute after ach meal at least twice a day (or as directed by a dentist or physician)
• Do not swallow

Children under 12 years of age: ask a dentist

Other Information

• Everest enamel was specially formulated to prevent surface stains on the teeth, which otherwise can occur while using Stannous Fluoride.

• Adequate tooth brushing may also prevent Stannous Fluoride stains which are not harmful or permanent and can be removed by a Dentist

Inactive Ingredients

Water, Sorbitol, Hydrated Silica, Xylitol, Glycerin, Sodium Gluconate, Flavor, Zinc Citrate, Quillaja Saponica Bark Extract, Cocamidopropyl Betaine, Titanium Dioxide, Smilax Aristolochiaefolia Root Extract, Sodium Hydroxide, Sodium Hydroxide, Sodium Tripolyphosphate, Tocopheryl Acetate, Xanthan Gum, Natural Menthol, Yucca Schidigera Rooth Extract, Dioscorea Villosa Root Extract

Questions or comments?

Call toll free 1-800-553-3682

Manufactured for:

Alpine Dental, Inc.

Brooklyn, NY 11218

Made in the USA

Item Code 1520-10

Evernamel

Brush Your Way To a Brighter Smile

Fresh Spearmint

Evernamel

Toothpaste with Remineralizing Benefits

Anticavity / Antigingivitis / Sensitivity Relief

122 g / 4.3 oz.